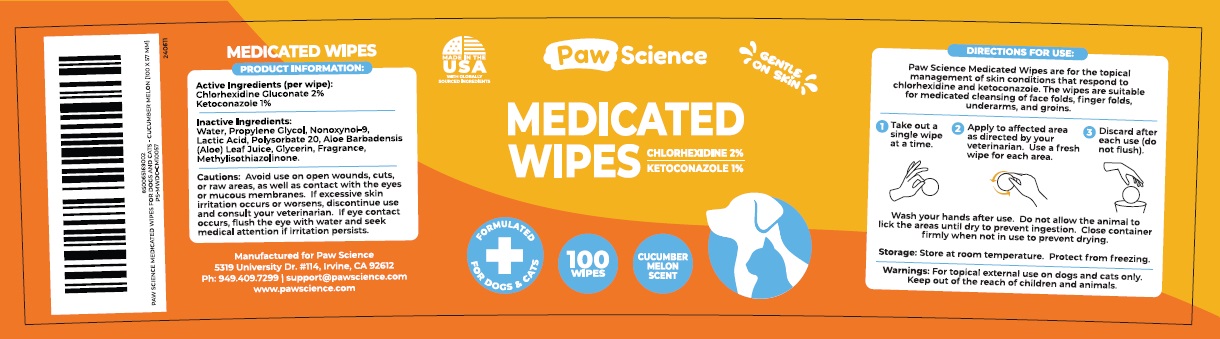 DRUG LABEL: Paw Science MEDICATED WIPES
NDC: 86207-001 | Form: CLOTH
Manufacturer: Pet Science LLC
Category: animal | Type: OTC ANIMAL DRUG LABEL
Date: 20240826

ACTIVE INGREDIENTS: CHLORHEXIDINE GLUCONATE 20 mg/1 mL; KETOCONAZOLE 10 mg/1 mL
INACTIVE INGREDIENTS: WATER; PROPYLENE GLYCOL; NONOXYNOL-9; LACTIC ACID, UNSPECIFIED FORM; POLYSORBATE 20; ALOE VERA LEAF; GLYCERIN; METHYLISOTHIAZOLINONE

Paw Science MEDICATED WIPES

Active Ingredients (per wipe):

Chlorhexidine Gluconate 2%
Ketoconazole 1%

Inactive Ingredients:

Water, Propylene Glycol, Nonoxynol-9, Lactic Acid, Polysorbate 20, Aloe Barbadensis (Aloe) Leaf Juice, Glycerin, Fragrance, Methylisothiazolinone.

Cautions:

Avoid use on open wounds, cuts, or raw areas, as well as contact with the eyes or mucous membranes. If excessive skin irritation occurs or worsens, discontinue use and consult your veterinarian. If eye contact occurs, flush the eye with water and seek medical attention if irritation persists.

DIRECTIONS FOR USE:

Paw Science Medicated Wipes are for the topical management of skin conditions that respond to chlorhexidine and ketoconazole. The wipes are suitable for medicated cleansing of face folds, finger folds, underarms, and groins.

1 Take out a single wipe at a time.
2 Apply to affected area as directed by your veterinarian. Use a fresh wipe for each area.
3 Discard after each use (do not flush).

Wash your hands after use. Do not allow the animal to lick the areas until dry to prevent ingestion. Close container firmly when not in use to prevent drying.

Storage:

Store at room temperature. Protect from freezing.

Warnings:

For topical external use on dogs and cats only. Keep out of the reach of children and animals.

MADE IN THE USA
WITH GLOBALLY SOURCED INGREDIENTS

GENTLE ON SKIN

FORMULATED FOR DOGS & CATS

CUCUMBER MELON SCENT

Manufactured for Paw Science
5319 University Dr. #114, Irvine, CA 92612
Ph: 949.409.7299 | support@pawscience.com
www.pawscience.com